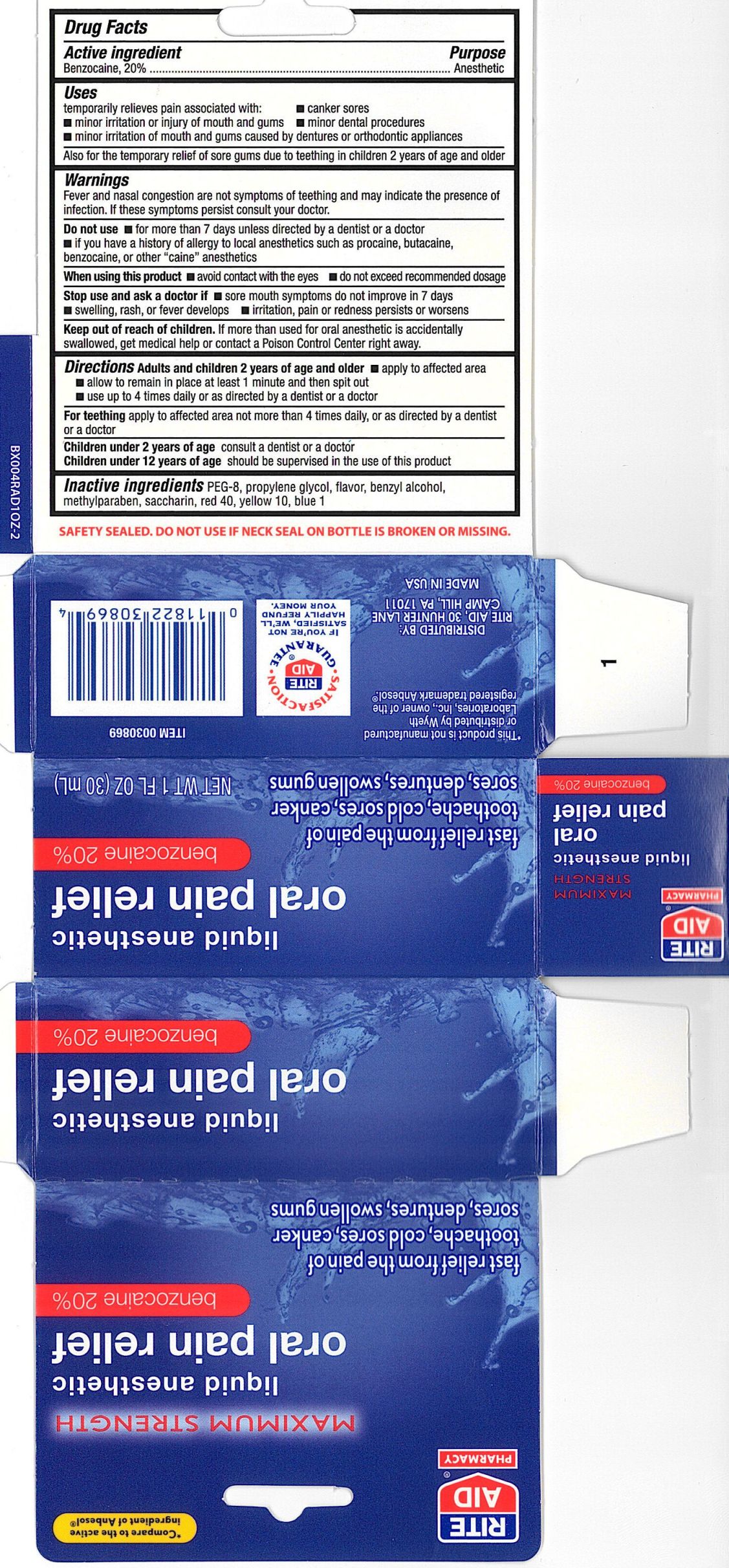 DRUG LABEL: Rite Aid Liquid Anesthetic Oral Pain Relief
NDC: 11822-3950 | Form: GEL
Manufacturer: Rite Aid Corporation
Category: otc | Type: HUMAN OTC DRUG LABEL
Date: 20100708

ACTIVE INGREDIENTS: BENZOCAINE 200 mg/1 mL
INACTIVE INGREDIENTS: BENZYL ALCOHOL; D&C YELLOW NO. 10; FD&C RED NO. 40; SPEARMINT OIL; PEPPERMINT OIL; METHYLPARABEN; POLYETHYLENE GLYCOL 400; PROPYLENE GLYCOL; SACCHARIN

drug facts

Active ingredient Purpose
Benzocaine, 20%............................................Anesthetic

Uses
- temporary relieves pain associated with: - canker sores
- minor irritation or injury of mouth and gums - minor dental procedures
- minor irritation of mouth and gums caused by dentures or orthodontic appliances
also for the temporary relief of sore gums due to teething in children 2 years of age and older

Keep out of reach of children. If more than is used for oral anesthetic is accidentally
swallowed, get medical help or contact a Poison Control Center right away.

Uses
- temporary relieves pain associated with: - canker sores
- minor irritation or injury of mouth and gums - minor dental procedures
- minor irritation of mouth and gums caused by dentures or orthodontic appliances
also for the temporary relief of sore gums due to teething in children 2 years of age and older

Warnings
Fever and nasal congestion are not symptoms of teething and may indicate the presence
of infection. If these symptoms persist, contact your doctor.
Do not use - for more than directed - for more than 7 days, unless directed by a dentist or doctor
- if you have a history of allergy to local anesthetics such as procaine, butacaine, benzocaine, or
other "caine" anesthetics
When using this product- avoid contact with the eyes - do not exceed recommended dosage
Stop use and ask a doctor if:
- sore mouth symptoms do not improve in 7 days
- swelling, rash or fever develops - irritation, pain or redness persists or worsens
Keep out of reach of children.If more then used for oral anesthetic is accidentally swallowed,
get medical help or contact a Poison Control Center right away.

DOSAGE AND ADMINISTRATION

Directions Adults and children 2 years of age and older
- apply to the affected area - allow to remain in place at least 1 minute and then spit out
- use up to four times a day or as directed by a dentist or doctor
For teething apply to affected area not more than 4 times dialy, or as directed by a dentist or doctor
Children under 2 years of age consult a dentist or doctor
Children under 12 years of age should be supervised in the use of this product

Inactive Ingredients
PEG-8, propylene glycol, flavor, benzyl alcohol, methylparaben, saccharin, red 40, yellow 10, blue 1